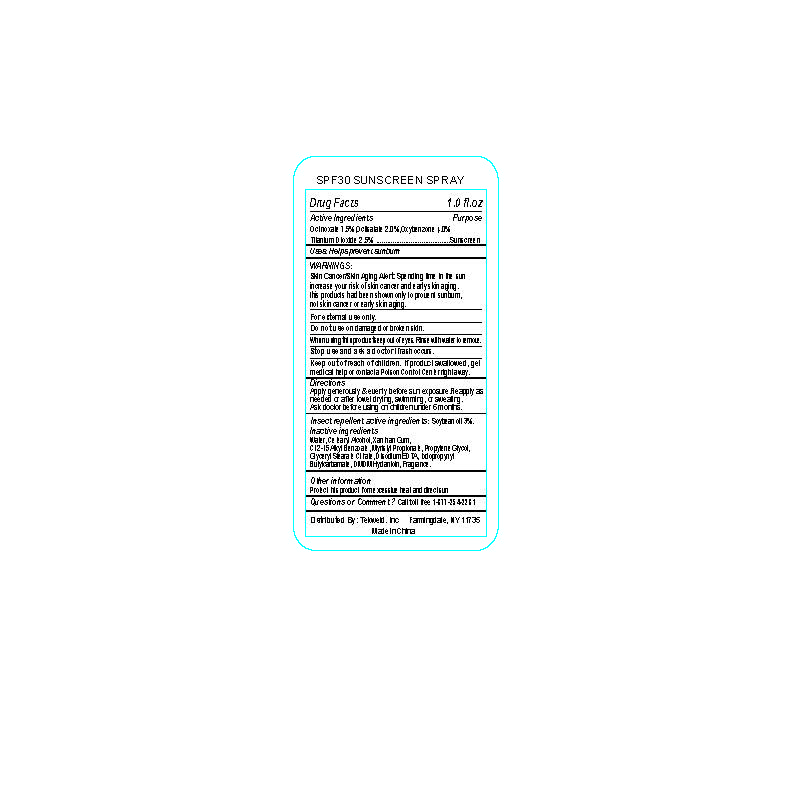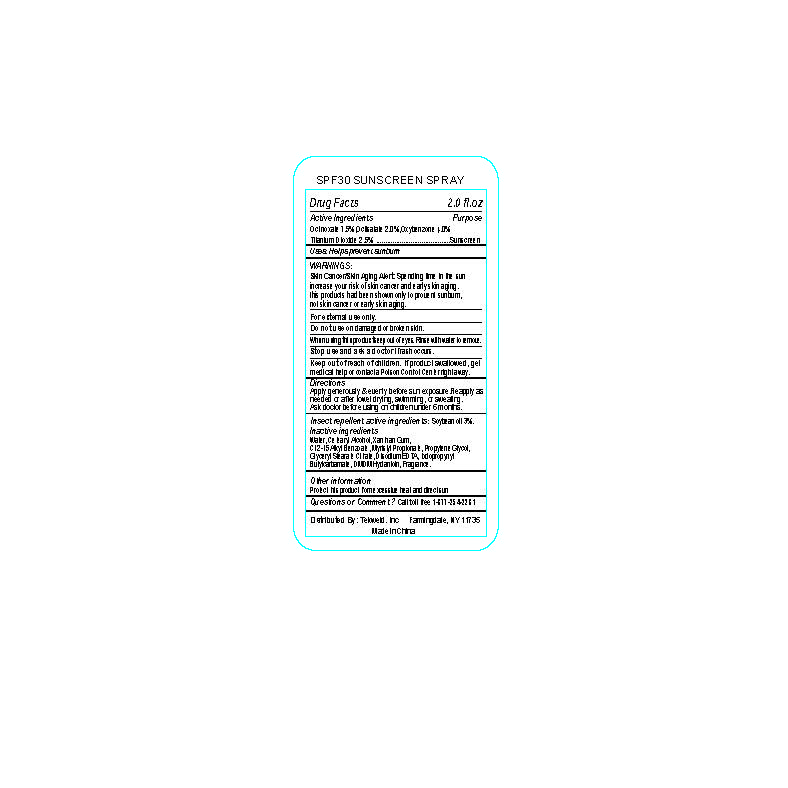 DRUG LABEL: SPF 30 SUNSCREEN
NDC: 31190-330 | Form: SPRAY
Manufacturer: Shanghai Kejing Cleaning Products Co., Ltd.
Category: otc | Type: HUMAN OTC DRUG LABEL
Date: 20160717

ACTIVE INGREDIENTS: OCTINOXATE 7.5 g/100 g; SOYBEAN OIL 3.0 g/100 g; OCTISALATE 2.0 g/100 g; OXYBENZONE 4.0 g/100 g; TITANIUM DIOXIDE 2.5 g/100 g
INACTIVE INGREDIENTS: WATER; CETOSTEARYL ALCOHOL; XANTHAN GUM; ALKYL (C12-15) BENZOATE; MYRISTYL PROPIONATE; PROPYLENE GLYCOL; GLYCERYL STEARATE CITRATE; EDETATE DISODIUM; IODOPROPYNYL BUTYLCARBAMATE; DMDM HYDANTOIN

Active Ingredients

Octinoxate 7.5%, Octisalate 2.0%, Oxybenzone 4.0%,

Titanium Dioxide 2.5%

Purpose

Sunscreen

INDICATIONS AND USAGE

Uses: Helps prevent sunburn

WARNINGS:

Skin Cancer/Skin Aging Alert: Spending time in the sun

increase your risk of skin cancer and early skin aging.

this product had been shown only to prevent sunburn,

not skin cancer or skin aging.

For external use only.

Do not use on damaged or broken skin.

When using this product keep out of eyes. Rinse with water to remove.

Stop use and ask a doctor if rash occurs.

Keep out of reach of children. If product swallowed, get

medical help or contact a Poison Control Center right away.

Directions

Apply generously & evenly before sun exposure. Reapply as

needed or after towel drying, swimming or sweating.

Ask doctor before using on children under 6 months.

Inactive ingredients

Water, Cetearyl Alcohol, Xanthan Gum,

C12-15 Alkyl Benzoate, Myristyl Propionate, Propylene Glycol,

Glyceryl Stearate Citrate, Disodium EDTA, Iodopropynyl

Butylcarbamate, DMDM Hydantoin, Fragrance

Other information

Protect this product from excessive heat and direct sun

QUESTIONS

Questions or Comment? Call toll free 1-877-254-2281

Insect repellent active ingredients: soybean oil 3%